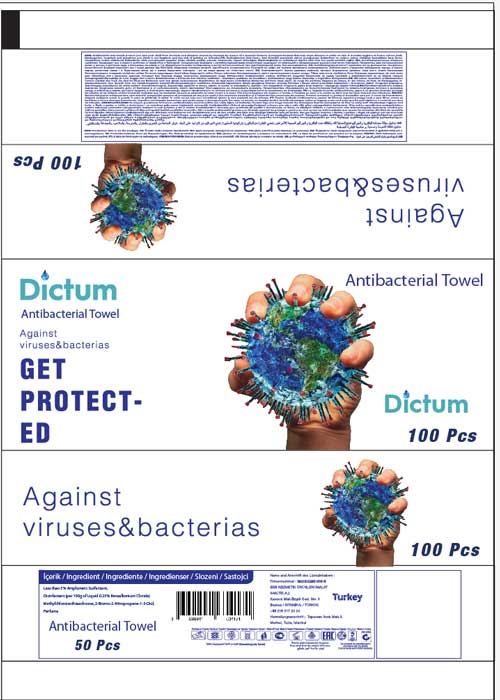 DRUG LABEL: Dictum Antibacterial Towel
NDC: 79780-105 | Form: SWAB
Manufacturer: BEB Kozmetik Urunleri Imalat Sanayi Ticaret AS
Category: otc | Type: HUMAN OTC DRUG LABEL
Date: 20201123

ACTIVE INGREDIENTS: BENZALKONIUM CHLORIDE 0.2 g/100 g; DIDECYLDIMONIUM CHLORIDE 0.05 g/100 g
INACTIVE INGREDIENTS: WATER; FRAGRANCE CLEAN ORC0600327 0.25 g/100 g

Purpose

Antiseptic: Hand Sanitizer Swab
Hand Sanitizer Swab to help reduce bacteria that potentially can cause disease. For use when soap and water are not available.

When using this product keep out of eyes, ears, and mouth. In case of contact with eyes, rinse eyes
thoroughly with warter.
Stop use and ask a doctor if irritation or rash occurs. These may be signs of a serious contiditon.
Keep our of reac of children. If swallowed, get medical help or contact a Poison Control Center right
away.
Stop use and ask a doctor if irritation or rash occurs. These may be signs of a serious condition.
Keep out of reach of children. If swallowed, get medical help or contact a Poison Control Center right
away.
Place enough product on hands to cover all surfaces. Rub hand together until dry.
Supervise children under 6 years of age when using this product to avoid swallowing.
Store between 15-43C (59-110F)
Avoid freezing and excessive heat above 43C (110F)

When using this product keep out of eyes, ears, and mouth. In case of contact with eyes, rinse eyes
thoroughly with warter.

Stop use and ask a doctor if irritation or rash occurs. These may be signs of a serious condition.

Keep out of reach of children. If swallowed, get medical help or contact a Poison Control Center right
away.
Stop use and ask a doctor if irritation or rash occurs. These may be signs of a serious condition.
Keep out of reach of children. If swallowed, get medical help or contact a Poison Control Center right
away.

KEEP OUT OF REACH OF CHILDREN

Keep our of reach of children. If swallowed, get medical help or contact a Poison Control Center right
away.

Active Ingredients

BENZALKONIUM CHLORIDE 0.2 g

DIDECYLDIMONIUM CHLORIDE 0.05 g

Inactive Ingredients

WATER

FRAGRANCE CLEAN 0.25 g

Warnings

For external use only. Flammable. Keep away from the heat of the flame.

Dosage

BENZALKONIUM CHLORIDE F5UM2KM3W7 0.2 g ACTIB

DIDECYLDIMONIUM CHLORIDE JXN40O9Y9B 0.05 g ACTIB

WATER 059QF0KO0R IACT

FRAGRANCE CLEAN ORC0600327 329LCV5BTF 0.25 gIACT